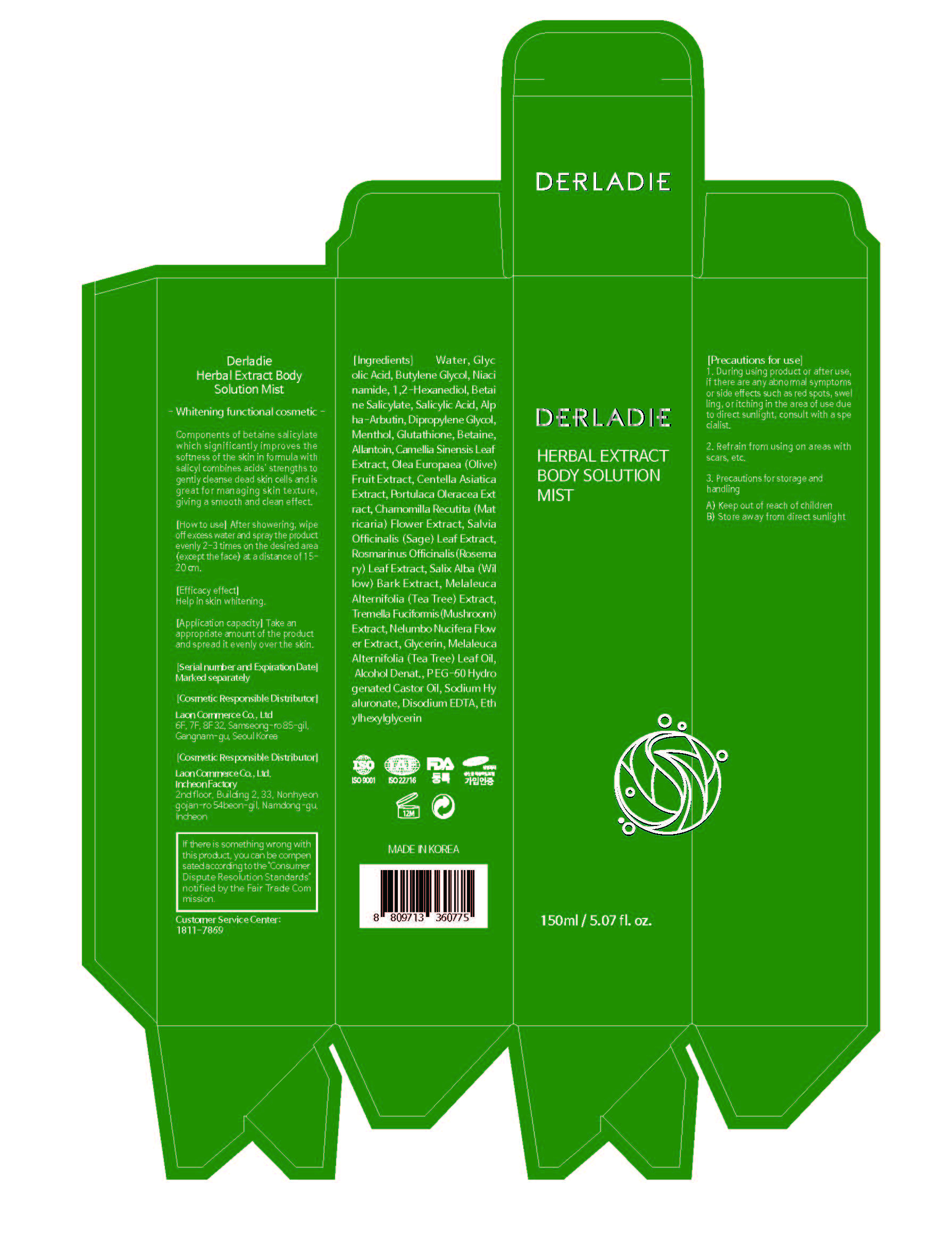 DRUG LABEL: DERLADIE HerbalExtract BodySolution MIST
NDC: 82083-0023 | Form: LIQUID
Manufacturer: LAON COMMERCE co ltd
Category: otc | Type: HUMAN OTC DRUG LABEL
Date: 20230728

ACTIVE INGREDIENTS: NIACINAMIDE 3 g/100 mL
INACTIVE INGREDIENTS: ALLANTOIN; GLYCERIN; WATER; CENTELLA ASIATICA

ACTIVE INGREDIENT

Niacinamide

INACTIVE INGREDIENT

Water
Glycolic Acid
Butylene Glycol
1,2-Hexanediol
Betaine Salicylate
Salicylic Acid
Alpha-Arbutin
Dipropylene Glycol
Menthol
Glutathione
Betaine
Allantoin
Camellia Sinensis Leaf Extract
Olea Europaea (Olive) Fruit Extract
Centella Asiatica Extract
Portulaca Oleracea Extract
Chamomilla Recutita (Matricaria) Flower Extract
Salvia Officinalis (Sage) Leaf Extract
Rosmarinus Officinalis (Rosemary) Leaf Extract
Salix Alba (Willow) Bark Extract
Melaleuca Alternifolia (Tea Tree) Extract
Tremella Fuciformis (Mushroom) Extract
Nelumbo Nucifera Flower Extract
Glycerin
Melaleuca Alternifolia (Tea Tree) Leaf Oil
Alcohol Denat.
PEG-60 Hydrogenated Castor Oil
Sodium Hyaluronate
Disodium EDTA
Ethylhexylglycerin

PURPOSE

skin protect

KEEP OUT OF REACH OF THE CHILDREN

INDICATIONS AND USAGE

After showering, wipe off excess water and spray the product evenly 2-3 times on the desired area (except the face) at a distance of 15-20cm.

WARNINGS

1. During using product or after use, if there are any abnormal symptoms or side effects such as red spots, swelling or itching in the area of use due to direct sunlight, consult with a specialist.

2. Refrain from using on areas with scars, etc.

3. Precautions for storage and handling

A) Keep out of reach of children

B) Store away from direct sunlight

DOSAGE AND ADMINISTRATION

topical use only